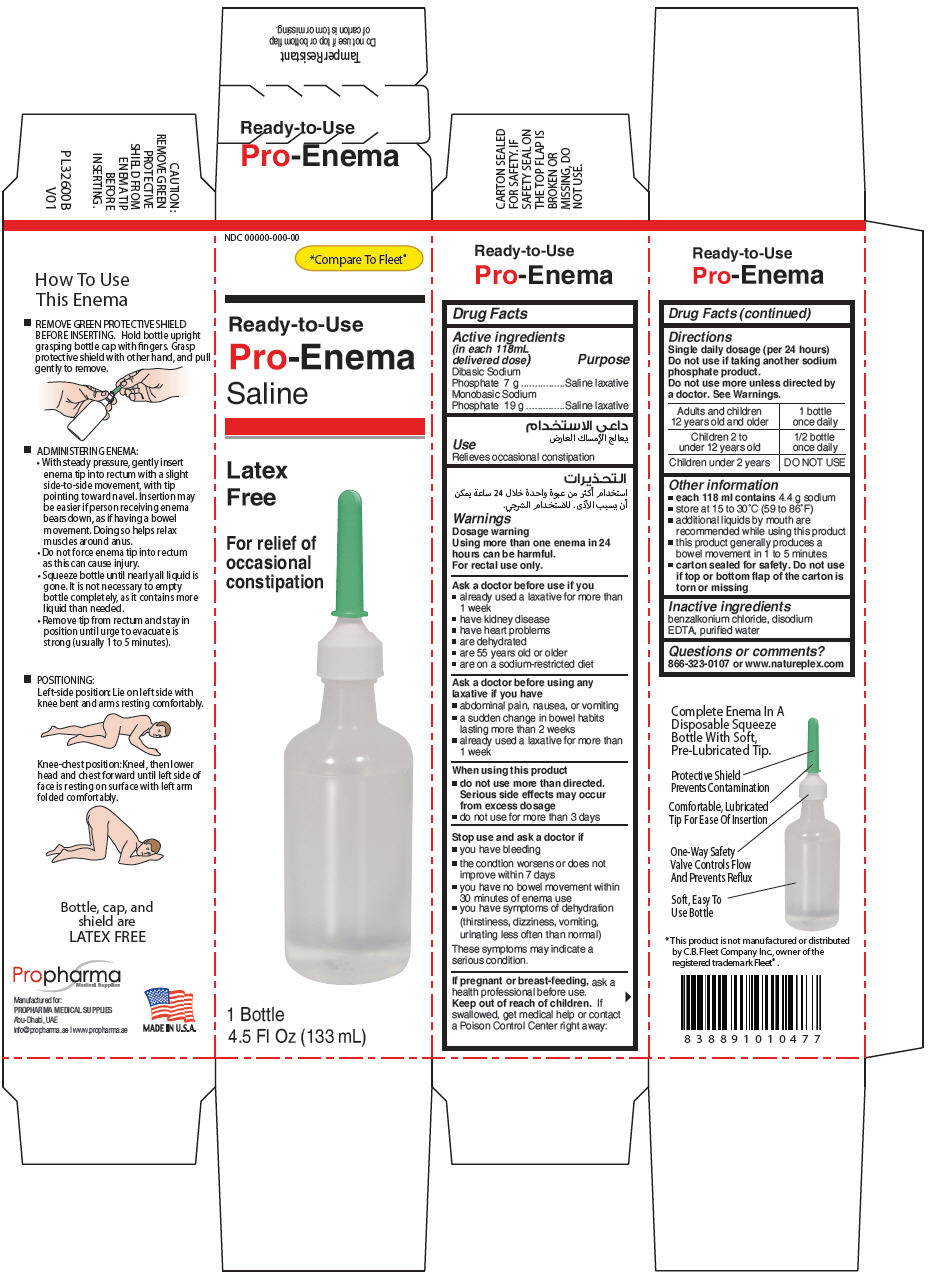 DRUG LABEL: Pro-Enema Single Saline  
NDC: 71451-001 | Form: ENEMA
Manufacturer: Propharma Medical Supplies
Category: otc | Type: HUMAN OTC DRUG LABEL
Date: 20170608

ACTIVE INGREDIENTS: Sodium Phosphate, Dibasic 7 g/118 mL; SODIUM PHOSPHATE, MONOBASIC, UNSPECIFIED FORM 19 g/118 mL
INACTIVE INGREDIENTS: BENZALKONIUM CHLORIDE; Edetate Disodium Anhydrous; Water

Pro-Enema Single Saline Enema
Laxative

Drug Facts

ACTIVE INGREDIENT

Active ingredients (in each 118mL delivered dose) | Purpose
Dibasic Sodium Phosphate 7 g | Saline laxative
Monobasic Sodium Phosphate 19 g | Saline laxative

Use

Relieves occasional constipation

Warnings

Dosage warning

Using more than one enema in 24 hours can be harmful.

For rectal use only.

Ask a doctor before use if you

- already used a laxative for more than 1 week
- have kidney disease
- have heart problems
- are dehydrated
- are 55 years old or older
- are on a sodium-restricted diet

Ask a doctor before using any laxative if you have

- abdominal pain, nausea, or vomiting
- a sudden change in bowel habits lasting more than 2 weeks
- already used a laxative for more than 1 week

When using this product

- do not use more than directed. Serious side effects may occur from excess dosage
- do not use for more than 3 days

Stop use and ask a doctor if

- you have bleeding
- the condtion worsens or does not improve within 7 days
- you have no bowel movement within 30 minutes of enema use
- you have symptoms of dehydration (thirstiness, dizziness, vomiting, urinating less often than normal)

These symptoms may indicate a serious condition.

PREGNANCY OR BREAST FEEDING

If pregnant or breast-feeding, ask a health professional before use.

Keep out of reach of children. If swallowed, get medical help or contact a Poison Control Center right away:

Directions

Single daily dosage (per 24 hours)

Do not use if taking another sodium phosphate product.

Do not use more unless directed by a doctor. See Warnings.

Adults and children 12 years old and older | 1 bottle once daily
Children 2 to under 12 years old | 1/2 bottle once daily
Children under 2 years | DO NOT USE

Other information

- each 118 ml contains 4.4 g sodium
- store at 15 to 30°C (59 to 86°F)
- additional liquids by mouth are recommended while using this product
- this product generally produces a bowel movement in 1 to 5 minutes
- carton sealed for safety. Do not use if top or bottom flap of the carton is torn or missing

Inactive ingredients

benzalkonium chloride, disodium EDTA, purified water

Questions or comments?

866-323-0107 or www.natureplex.com

PRINCIPAL DISPLAY PANEL - 133 mL Bottle Carton

NDC 00000-000-00

*Compare To Fleet®

Ready-to-Use
Pro-Enema
Saline

Latex
Free

For relief of
occasional
constipation

1 Bottle
4.5 Fl Oz (133 mL)